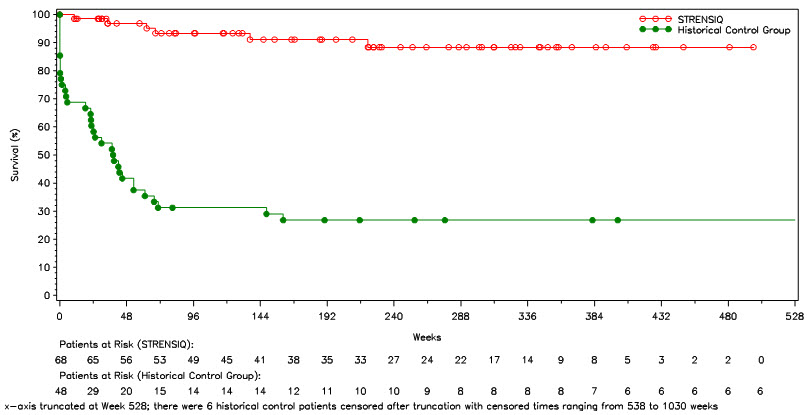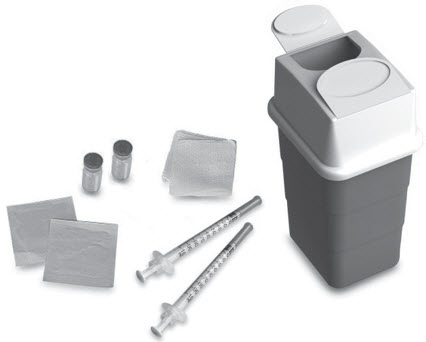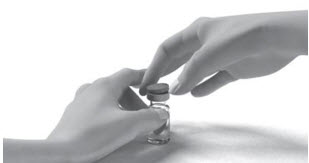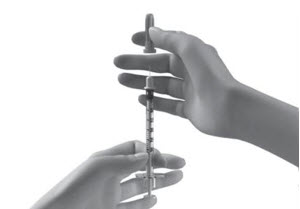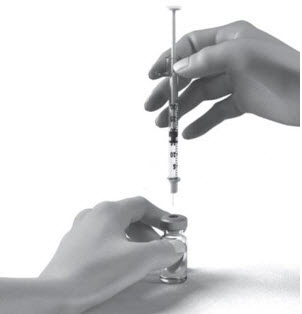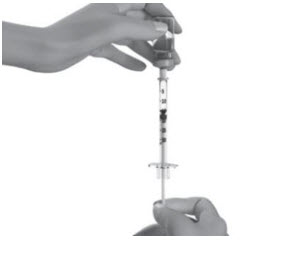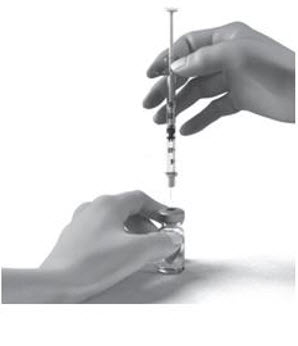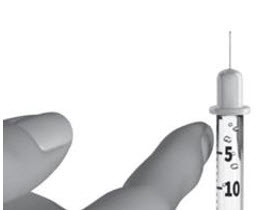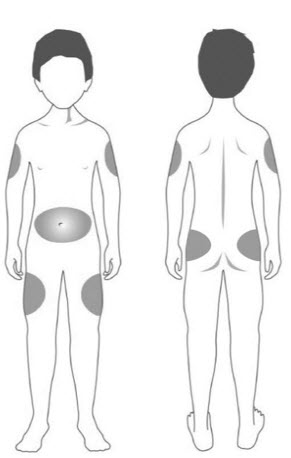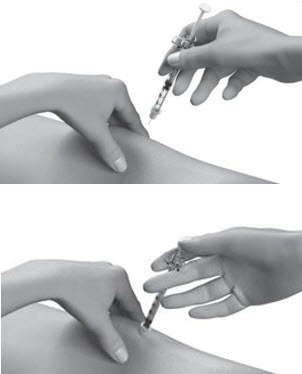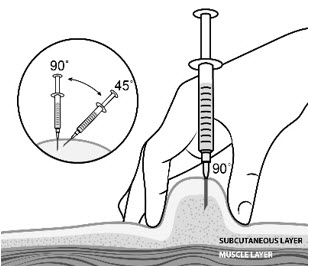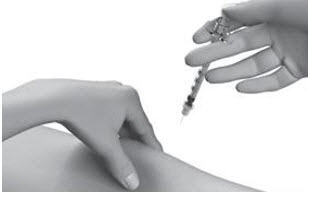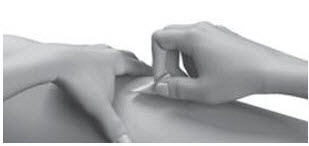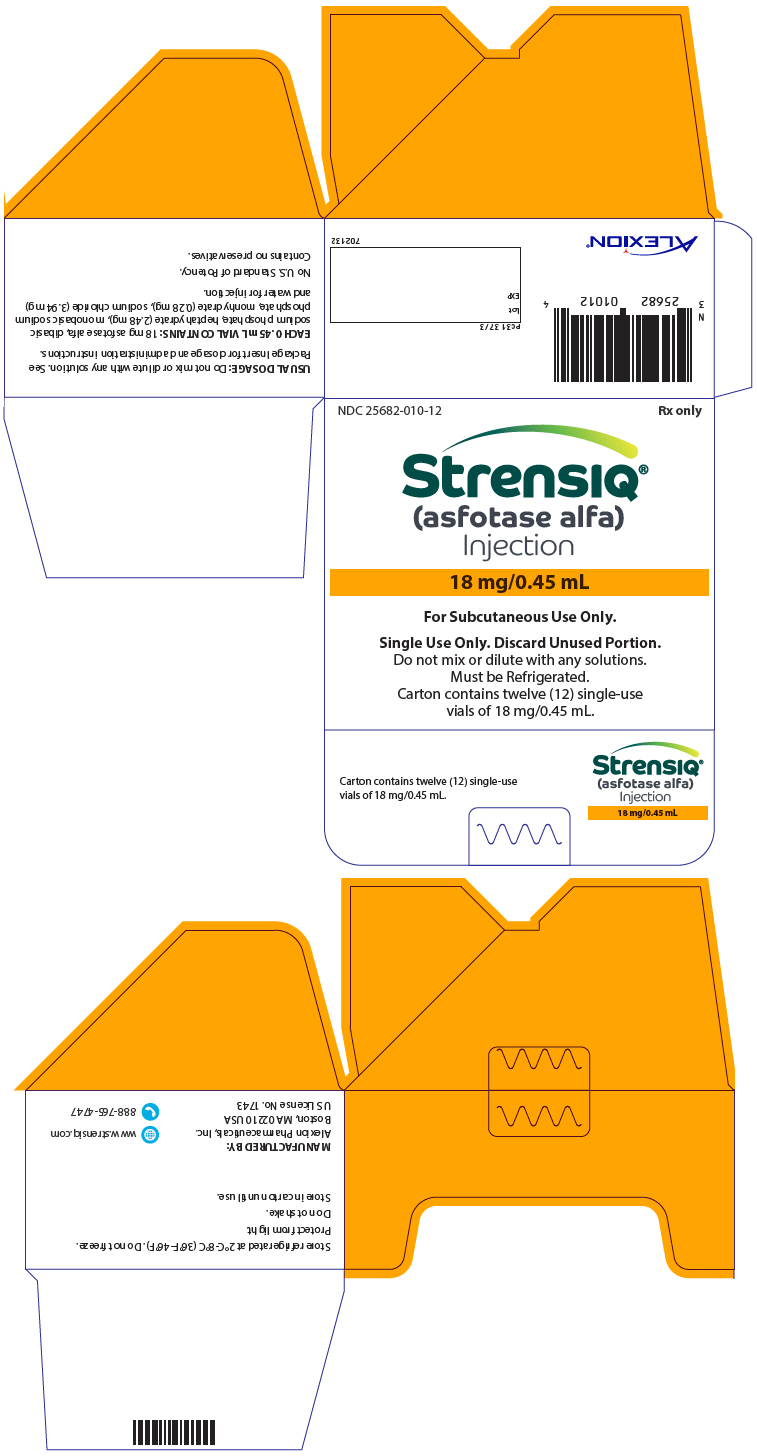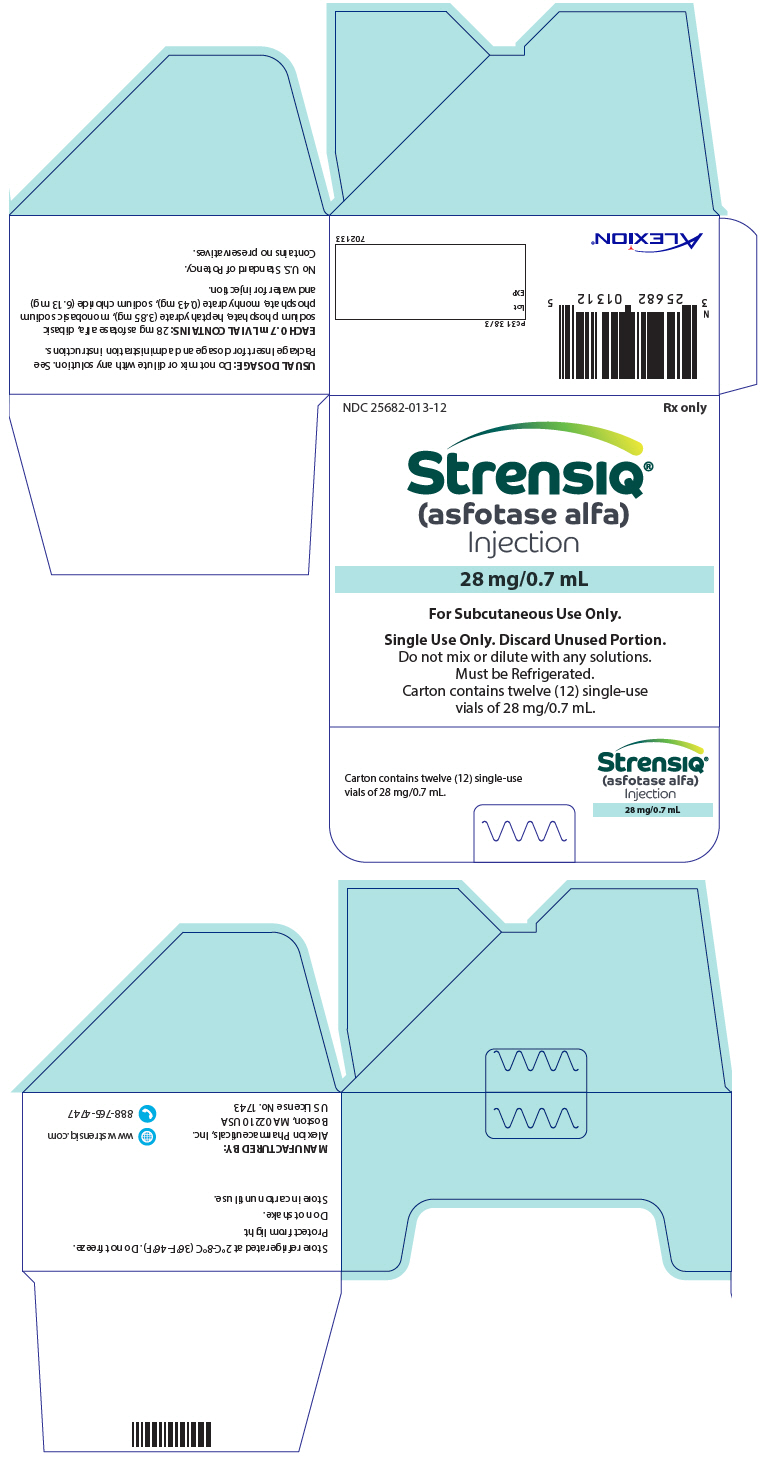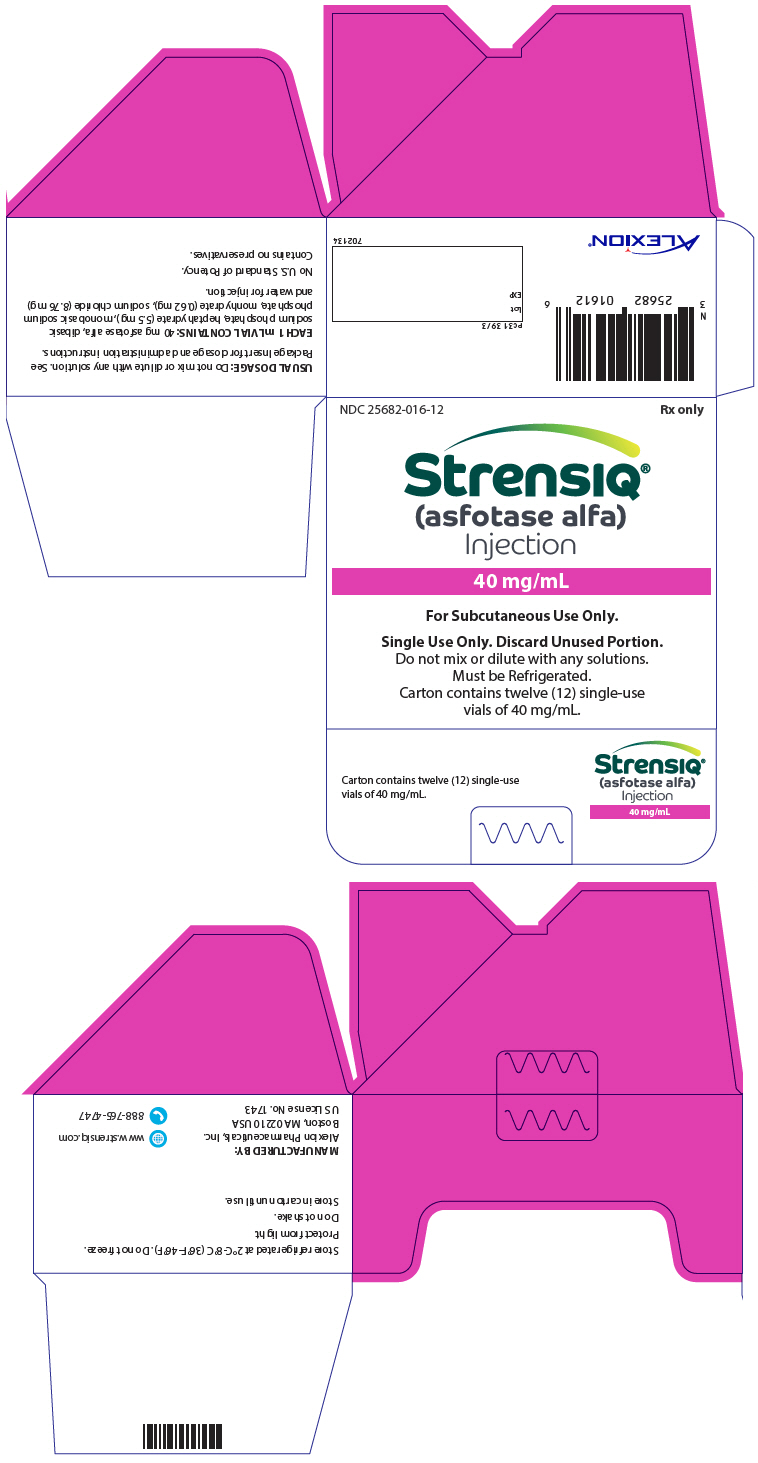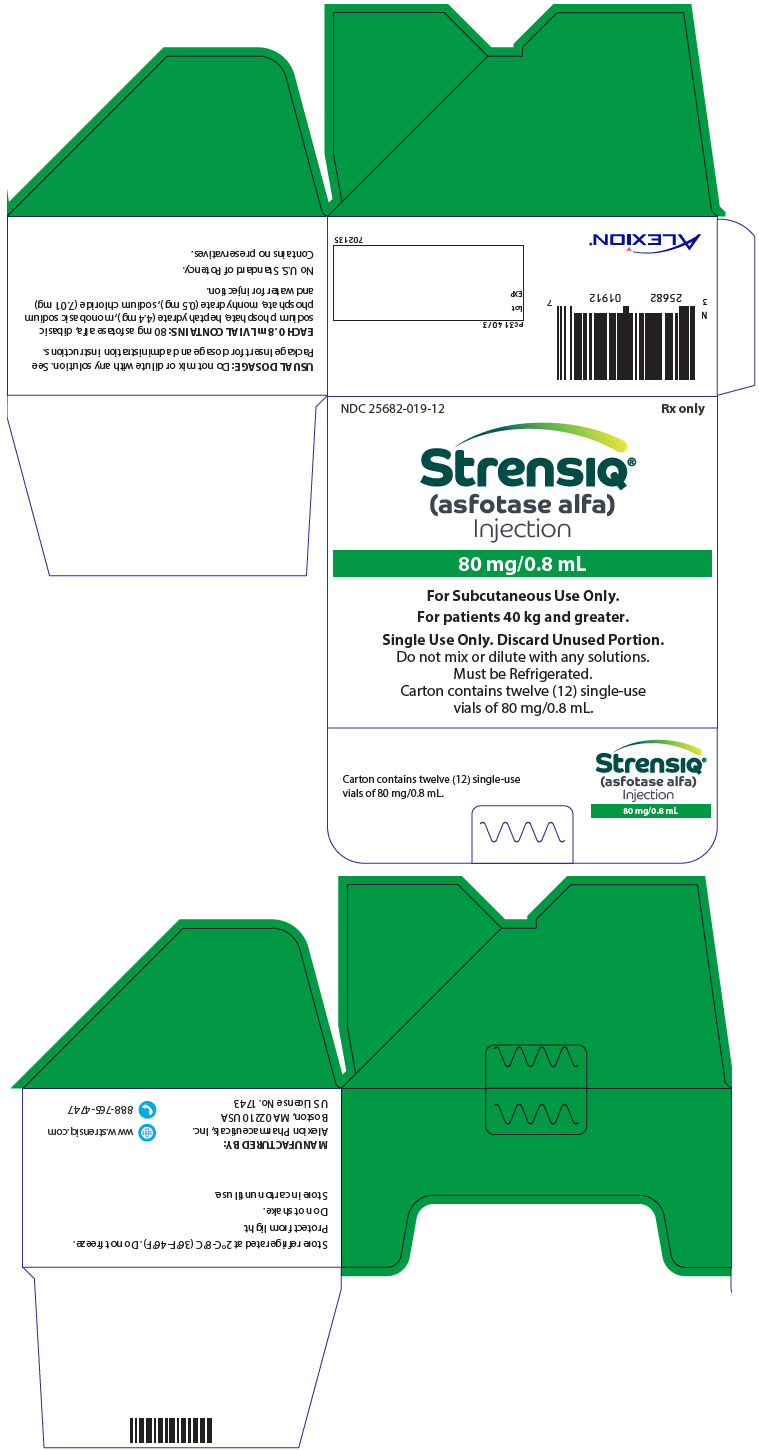 DRUG LABEL: STRENSIQ
NDC: 25682-010 | Form: SOLUTION
Manufacturer: Alexion Pharmaceuticals, Inc.
Category: prescription | Type: HUMAN PRESCRIPTION DRUG LABEL
Date: 20251212

ACTIVE INGREDIENTS: ASFOTASE ALFA 18 mg/0.45 mL
INACTIVE INGREDIENTS: SODIUM PHOSPHATE, DIBASIC, HEPTAHYDRATE 2.48 mg/0.45 mL; SODIUM PHOSPHATE, MONOBASIC, MONOHYDRATE 0.28 mg/0.45 mL; SODIUM CHLORIDE 3.94 mg/0.45 mL

HIGHLIGHTS OF PRESCRIBING INFORMATION

These highlights do not include all the information needed to use STRENSIQ safely and effectively. See full prescribing information for STRENSIQ.
STRENSIQ® (asfotase alfa) injection, for subcutaneous use
Initial U.S. Approval: 2015

WARNING: HYPERSENSITIVITY REACTIONS INCLUDING ANAPHYLAXIS

See full prescribing information for complete boxed warning.

- Anaphylaxis has occurred during the early course of enzyme replacement therapy and after extended duration of therapy. (5.1)
- Initiate STRENSIQ under the supervision of a healthcare provider with appropriate medical monitoring and support measures. (5.1)
- If a severe hypersensitivity reaction (e.g., anaphylaxis) occurs, discontinue STRENSIQ and immediately initiate appropriate medical treatment, including use of epinephrine. (5.1)

RECENT MAJOR CHANGES

Boxed Warning | 7/2024
Dosage and Administration (2.1) | 7/2024
Warnings and Precautions (5.1) | 7/2024

1 INDICATIONS AND USAGE

STRENSIQ is a tissue nonspecific alkaline phosphatase indicated for the treatment of patients with perinatal/infantile- and juvenile-onset hypophosphatasia (HPP). (1)

2 DOSAGE AND ADMINISTRATION

Perinatal/Infantile-Onset HPP (2.2)

- Recommended dosage regimen is 2 mg/kg administered subcutaneously three times per week, or 1 mg/kg administered six times per week. Injection site reactions may limit the tolerability of the six times per week regimen.
- The dose may be increased to 3 mg/kg three times per week for insufficient efficacy.

Juvenile-Onset HPP (2.3)

- Recommended dosage regimen is 2 mg/kg administered subcutaneously three times per week, or 1 mg/kg administered six times per week. Injection site reactions may limit the tolerability of the six times per week regimen.

Preparation and Weight-Based Dosing (2.4):

- Caution: Do not use the 80 mg/0.8 mL vial in pediatric patients weighing less than 40 kg because the systemic asfotase alfa exposure achieved with the 80 mg/0.8 mL vial (higher concentration) is lower than that achieved with the other strength vials (lower concentration). A lower exposure may not be adequate for this subgroup of patients.
- See full prescribing information for tables of weight-based dosing by treatment regimen.

Administration (2.5):

- For subcutaneous injection only.
- Rotate injection sites. Do not administer to areas that are reddened, inflamed or swollen.

3 DOSAGE FORMS AND STRENGTHS

Injection: 18 mg/0.45 mL, 28 mg/0.7 mL, 40 mg/mL, or 80 mg/0.8 mL solution in single-dose vials. (3)

4 CONTRAINDICATIONS

None. (4)

5 WARNINGS AND PRECAUTIONS

- Lipodystrophy: Localized reactions were reported after several months of treatment; follow proper injection technique and rotate injection sites. (5.2)
- Ectopic Calcifications (eye and kidneys): Monitor using ophthalmologic examinations and renal ultrasounds at baseline and periodically during treatment. (5.3)
- Possible Immune-Mediated Clinical Effects: Evaluate patients for antibody formation if clinically indicated. (5.4)

6 ADVERSE REACTIONS

Most common adverse reactions (≥ 10%) are injection site reactions, lipodystrophy, ectopic calcifications and hypersensitivity reactions. (6.1)
To report SUSPECTED ADVERSE REACTIONS, contact Alexion Pharmaceuticals, Inc. at 1-844-259-6783 or FDA at 1-800-FDA-1088 or www.fda.gov/medwatch.

7 DRUG INTERACTIONS

- Drug Interference with Laboratory Tests: Alkaline Phosphatase (ALP) is used as a detection reagent in many laboratory tests and the presence of asfotase alfa in clinical laboratory samples could result in erroneous test results. Inform laboratory personnel and discuss use of an alternative testing platform for patients on treatment. (7.1)
- Serum Alkaline Phosphatase: Serum ALP measurements are expected to be elevated during treatment and may be unreliable for clinical decision making. (7.1)

FULL PRESCRIBING INFORMATION

WARNING: HYPERSENSITIVITY REACTIONS INCLUDING ANAPHYLAXIS

Patients treated with enzyme replacement therapies have experienced life-threatening hypersensitivity reactions, including anaphylaxis. Anaphylaxis has occurred during the early course of enzyme replacement therapy and after extended duration of therapy.

Initiate STRENSIQ under the supervision of a healthcare provider with appropriate medical monitoring and support measures. If a severe hypersensitivity reaction (e.g., anaphylaxis) occurs, discontinue STRENSIQ and immediately initiate appropriate medical treatment, including use of epinephrine. Inform patients of the symptoms of life-threatening hypersensitivity reactions, including anaphylaxis and to seek immediate medical care should symptoms occur [see Warnings and Precautions (5.1)].

1 INDICATIONS AND USAGE

STRENSIQ® is indicated for the treatment of patients with perinatal/infantile- and juvenile-onset hypophosphatasia (HPP).

2 DOSAGE AND ADMINISTRATION

2.1 Recommendations Prior to STRENSIQ Treatment

Initiate STRENSIQ under the supervision of a healthcare provider with appropriate medical monitoring and support measures [see Warnings and Precautions (5.1)].

2.2 Dosage for Perinatal/Infantile-Onset HPP

The recommended dosage regimen of STRENSIQ for the treatment of perinatal/infantile-onset HPP is 6 mg/kg per week administered subcutaneously as either:

- 2 mg/kg three times per week, or
- 1 mg/kg six times per week. Injection site reactions may limit the tolerability of the six times per week regimen [see Adverse Reactions (6.1)].

The dose of STRENSIQ may be increased for lack of efficacy (e.g., no improvement in respiratory status, growth, or radiographic findings) up to 9 mg/kg per week administered subcutaneously as 3 mg/kg three times per week.

2.3 Dosage for Juvenile-Onset HPP

The recommended dosage regimen of STRENSIQ for the treatment of juvenile-onset HPP is 6 mg/kg per week administered subcutaneously as either:

- 2 mg/kg three times per week, or
- 1 mg/kg six times per week. Injection site reactions may limit the tolerability of the six times per week regimen [see Adverse Reactions (6.1)].

2.4 Preparation and Weight-Based Dosing Tables

Caution: Do not use the 80 mg/0.8 mL vial of STRENSIQ in pediatric patients weighing less than 40 kg because the systemic exposure of asfotase alfa achieved with the 80 mg/0.8 mL vial (higher concentration) is lower than that achieved with the other strength vials (lower concentration). A lower exposure may not be adequate for this subgroup of patients [see Dosage Forms and Strengths (3), Clinical Pharmacology (12.3)].

1. Determine the total weekly volume needed for the prescribed dosage based on the patient's weight and recommended dosage. Follow these steps to determine the patient dose.
  Total weekly dose (mg) = patient's weight (kg) × prescribed dose (mg/kg/week)
  Total injection volume (mL) per week = Total dose (mg/week) divided by the STRENSIQ concentration (40 mg/mL or 100 mg/mL). Note product concentrations are: 40 mg/mL (vial strengths 18 mg/0.45 mL, 28 mg/0.7 mL, 40 mg/mL) or 100 mg/mL (vial strength 80 mg/0.8 mL).
  Round total injection volume to the nearest hundredth of a mL
  Total number of vials per week = Total injection volume divided by vial volume (mL)
2. Determine the number of injection days per week (three or six per week).
3. Determine dose per injection day. Patient weights should be rounded to the nearest kilogram when determining dose. Use the following tables for guidance, for patients administering 2 mg/kg three times per week (Table 1), 1 mg/kg six times per week (Table 2) and for dose escalations to 3 mg/kg three times per week, recommended only for patients with perinatal/infantile-onset HPP [see Dosage and Administration (2.2)] (Table 3).

Table 1: Weight-Based Dosing for Administration of 2 mg/kg Three Times per Week
Body Weight (kg) [Do not use the 80 mg/0.8 mL vial of STRENSIQ in pediatric patients weighing less than 40 kg [see Clinical Pharmacology (12.3)].] | Dose to Inject | Volume to Inject | Vial Configuration
3 | 6 mg | 0.15 mL | 18 mg/0.45 mL
4 | 8 mg | 0.2 mL | 18 mg/0.45 mL
5 | 10 mg | 0.25 mL | 18 mg/0.45 mL
6 | 12 mg | 0.3 mL | 18 mg/0.45 mL
7 | 14 mg | 0.35 mL | 18 mg/0.45 mL
8 | 16 mg | 0.4 mL | 18 mg/0.45 mL
9 | 18 mg | 0.45 mL | 18 mg/0.45 mL
10 | 20 mg | 0.5 mL | 28 mg/0.7 mL
15 | 30 mg | 0.75 mL | 40 mg/1 mL
20 | 40 mg | 1 mL | 40 mg/1 mL
25 | 50 mg | 1.25 mL | Two 28 mg/0.7 mL vials
30 | 60 mg | 1.5 mL | Two 40 mg/1 mL vials
35 | 70 mg | 1.75 mL | Two 40 mg/1 mL vials
40 | 80 mg | 0.8 mL | 80 mg/0.8 mL
50 | 100 mg | 1 mL | Two 80 mg/0.8 mL vials
60 | 120 mg | 1.2 mL [When preparing a volume for injection greater than 1 mL, split the volume equally between two syringes, and administer two injections. When administering the two injections, use two separate injection sites.] | Two 80 mg/0.8 mL vials
70 | 140 mg | 1.4 mL | Two 80 mg/0.8 mL vials
80 | 160 mg | 1.6 mL | Two 80 mg/0.8 mL vials

Table 2: Weight-Based Dosing for Administration of 1 mg/kg Six Times per Week
Body Weight (kg) [Do not use the 80 mg/0.8 mL vial of STRENSIQ in pediatric patients weighing less than 40 kg [see Clinical Pharmacology (12.3)].] | Dose to Inject | Volume to Inject | Vial Configuration
3 | 3 mg | 0.08 mL | 18 mg/0.45 mL
4 | 4 mg | 0.1 mL | 18 mg/0.45 mL
5 | 5 mg | 0.13 mL | 18 mg/0.45 mL
6 | 6 mg | 0.15 mL | 18 mg/0.45 mL
7 | 7 mg | 0.18 mL | 18 mg/0.45 mL
8 | 8 mg | 0.2 mL | 18 mg/0.45 mL
9 | 9 mg | 0.23 mL | 18 mg/0.45 mL
10 | 10 mg | 0.25 mL | 18 mg/0.45 mL
15 | 15 mg | 0.38 mL | 18 mg/0.45 mL
20 | 20 mg | 0.5 mL | 28 mg/0.7 mL
25 | 25 mg | 0.63 mL | 28 mg/0.7 mL
30 | 30 mg | 0.75 mL | 40 mg/1 mL
35 | 35 mg | 0.88 mL | 40 mg/1 mL
40 | 40 mg | 1 mL | 40 mg/1 mL
50 | 50 mg | 0.5 mL | 80 mg/0.8 mL
60 | 60 mg | 0.6 mL | 80 mg/0.8 mL
70 | 70 mg | 0.7 mL | 80 mg/0.8 mL
80 | 80 mg | 0.8 mL | 80 mg/0.8 mL
90 | 90 mg | 0.9 mL | Two 80 mg/0.8 mL vials
100 | 100 mg | 1 mL | Two 80 mg/0.8 mL vials

Table 3: Weight-Based Dosing for Administration of 3 mg/kg Three Times per Week – Only for Perinatal/Infantile-Onset HPP [A regimen of 3 mg/kg three times per week is recommended only for patients with perinatal/infantile-onset HPP [see Dosage and Administration (2.2)]]
Body Weight (kg) [Do not use the 80 mg/0.8 mL vial of STRENSIQ in pediatric patients weighing less than 40 kg [see Clinical Pharmacology (12.3)].] | Dose to Inject | Volume to Inject | Vial Configuration
3 | 9 mg | 0.23 mL | 18 mg/0.45 mL
4 | 12 mg | 0.3 mL | 18 mg/0.45 mL
5 | 15 mg | 0.38 mL | 18 mg/0.45 mL
6 | 18 mg | 0.45 mL | 18 mg/0.45 mL
7 | 21 mg | 0.53 mL | 28 mg/0.7 mL
8 | 24 mg | 0.6 mL | 28 mg/0.7 mL
9 | 27 mg | 0.68 mL | 28 mg/0.7 mL
10 | 30 mg | 0.75 mL | 40 mg/1 mL
15 | 45 mg | 1.13 mL [When preparing a volume for injection greater than 1 mL, split the volume equally between two syringes, and administer two injections. When administering the two injections, use two separate injection sites.] | Two 28 mg/0.7 mL vials
20 | 60 mg | 1.5 mL | Two 40 mg/1 mL vials
25 | 75 mg | 1.88 mL | Two 40 mg/1 mL vials

4. Take the unopened STRENSIQ vial(s) out of the refrigerator 15 to 30 minutes before injecting to allow the liquid to reach room temperature.
  Do not warm STRENSIQ in any other way (for example, do not warm it in a microwave or in hot water).
5. Inspect the solution in the vial(s) for particulate matter and discoloration. STRENSIQ is supplied as a clear, slightly opalescent or opalescent, colorless to slightly yellow aqueous solution; a few small translucent or white particles may be present. Discard any vial(s) not consistent with this appearance.
6. Assemble injection supplies. Administer STRENSIQ using sterile disposable 1 mL syringes and ½ inch injection needles, between 25 to 29 gauge are recommended. The use of two different gauge needles is recommended, a larger bore needle (e.g. 25 gauge) for withdrawal of the medication, and a smaller bore needle (e.g. 29 gauge) for the injection. For doses greater than 1 mL, the injection volume should be split equally between two 1 mL syringes. Always use a new syringe and needle for each injection.
7. Remove vial cap, aseptically prepare the vial and insert the syringe into the vial to withdraw the prescribed dose for administration. Do not shake.
8. Remove any air bubbles in the syringe and verify the correct dose.
9. STRENSIQ vials are for one time use only. Discard any unused product.

2.5 Administration

STRENSIQ is for subcutaneous injection only.

- When administering two injections, use two separate injection sites.
- Administer STRENSIQ within 3 hours upon removal of the vial(s) from refrigeration.
- Rotate the injection from among the following sites to reduce the risk of lipodystrophy: abdominal area, thigh, deltoid, or buttocks [see Warnings and Precautions (5.2), Adverse Reactions (6.1)].
- Do NOT administer injections in areas that are reddened, inflamed, or swollen.
- Inject STRENSIQ subcutaneously into the determined site and properly dispose of the syringe and the needle.

3 DOSAGE FORMS AND STRENGTHS

STRENSIQ is a clear, slightly opalescent or opalescent, colorless to slightly yellow aqueous solution; few small translucent or white particles may be present. The product is available as:

- Injection: 18 mg/0.45 mL, 28 mg/0.7 mL, 40 mg/mL, or 80 mg/0.8 mL solution in single-dose vials

4 CONTRAINDICATIONS

None.

5 WARNINGS AND PRECAUTIONS

5.1 Hypersensitivity Reactions Including Anaphylaxis

Life-threatening hypersensitivity reactions, including anaphylaxis, have been reported in patients treated with enzyme replacement therapies, including STRENSIQ. Signs and symptoms consistent with anaphylaxis included difficulty breathing, choking sensation, nausea, periorbital edema, and dizziness. These reactions have occurred within minutes after subcutaneous administration of STRENSIQ and have been observed more than 1 year after treatment initiation. Other hypersensitivity reactions have also been reported in STRENSIQ-treated patients, including vomiting, fever, headache, flushing, irritability, chills, erythema, rash, pruritus and oral hypoesthesia [see Adverse Reactions (6.1)].

Anaphylaxis has occurred during the early course of enzyme replacement therapy and after extended duration of therapy. Initiate STRENSIQ under the supervision of a healthcare provider with appropriate medical monitoring and support measures. If a severe hypersensitivity reaction (e.g., anaphylaxis) occurs, discontinue STRENSIQ and immediately initiate appropriate medical treatment, including use of epinephrine. Consider the risks and benefits of re-administering STRENSIQ to individual patients following a severe reaction. If the decision is made to re-administer the product, monitor patients for a reoccurrence of signs and symptoms of a severe hypersensitivity reaction. Inform patients of the symptoms of life-threatening hypersensitivity reactions, including anaphylaxis and to seek immediate medical care should symptoms occur.

5.2 Lipodystrophy

Localized lipodystrophy, including lipoatrophy and lipohypertrophy, has been reported at injection sites after several months in patients treated with STRENSIQ in clinical trials [see Adverse Reactions (6.1)]. Advise patients to follow proper injection technique and to rotate injection sites [see Dosage and Administration (2.5)].

5.3 Ectopic Calcifications

Patients with HPP are at increased risk for developing ectopic calcifications. Events of ectopic calcification, including ophthalmic (conjunctival and corneal) and renal (nephrocalcinosis, nephrolithiasis), have been reported in the clinical trial experience with STRENSIQ. There was insufficient information to determine whether or not the reported events were consistent with the disease or due to STRENSIQ. No visual changes or changes in renal function were reported resulting from the occurrence of ectopic calcifications.

Ophthalmology examinations and renal ultrasounds are recommended at baseline and periodically during treatment with STRENSIQ to monitor for signs and symptoms of ophthalmic and renal ectopic calcifications and for changes in vision or renal function.

5.4 Possible Immune-Mediated Clinical Effects

In clinical trials, most STRENSIQ-treated patients developed anti-asfotase alfa antibodies and neutralizing antibodies which resulted in reduced systemic exposure of asfotase alfa [see Immunogenicity (6.2)]. In postmarketing reports, some STRENSIQ-treated patients with initial therapeutic response subsequently developed recurrence and worsening in disease-associated laboratory and radiographic biomarkers (some in association with neutralizing antibodies) suggesting possible immune-mediated effects on STRENSIQ's pharmacologic action resulting in disease progression [see Adverse Reactions (6.3)]. The effect of anti-asfotase alfa antibody formation on the long-term efficacy of STRENSIQ is unknown. There are no marketed anti-asfotase alfa antibody tests. If patients experience progression of HPP symptoms or worsening of disease-associated laboratory and imaging biomarkers after a period of initial therapeutic response to STRENSIQ, consider obtaining anti-asfotase alfa antibody testing by contacting STRENSIQ Medical Information at Alexion at 1-888-765-4747 or by email at medinfo@alexion.com. Close clinical follow up is recommended.

6 ADVERSE REACTIONS

The following adverse reactions are described below and elsewhere in the labeling:

- Hypersensitivity Reactions [see Warnings and Precautions (5.1)]
- Lipodystrophy [see Warnings and Precautions (5.2)]
- Ectopic Calcifications [see Warnings and Precautions (5.3)]
- Possible Immune-Mediated Clinical Effects [see Warnings and Precautions (5.4)]

6.1 Clinical Trials Experience

Because clinical trials are conducted under widely varying conditions, adverse reaction rates observed in the clinical trials of a drug cannot be directly compared to rates in the clinical trials of another drug and may not reflect the rates observed in practice.

The data described below reflect exposure to STRENSIQ in 99 patients with perinatal/infantile- or juvenile onset HPP (age 1 day to 58 years) treated with STRENSIQ, most for more than 2 years (range 1 day to 312 weeks [78 months]): 51 patients received at least 96 weeks (24 months) of treatment and 39 patients received 168 weeks (42 months) or more of treatment [see Clinical Studies (14)].

Common Adverse Reactions

Overall, the most common adverse reactions reported were injection site reactions (63%). Other common adverse reactions included lipodystrophy (28%), ectopic calcifications (14%), and hypersensitivity reactions (12%).

Table 4 summarizes the adverse reactions that occurred at a rate of at least 10% in clinical trials following subcutaneous injection of STRENSIQ by patient population and STRENSIQ dosage regimen.

The frequency of injection site reactions, lipodystrophy and ectopic calcification were higher in patients with juvenile-onset HPP as compared to perinatal/infantile-onset HPP patients.

The majority of injection site reactions resolved within a week. Two patients experienced injection site reactions that led to reductions of their STRENSIQ dose. One patient switched from six times per week dosing to 3 times per week dosing as a result of injection site reactions. One other patient experienced a severe injection site reaction of injection site discoloration and withdrew from the trial.

Table 4: Adverse Reactions Reported in at Least 10% of Patients with Perinatal/Infantile- or Juvenile-onset HPP Enrolled in STRENSIQ Clinical Trials
 | Perinatal/Infantile-onset HPP |  |  | Juvenile-onset HPP
Adverse Reaction Category or Term | STRENSIQ less than or equal to 6 mg/kg per week (N=66) n (%) | STRENSIQ more than 6 mg/kg/week [Adverse reactions are from the combined period of 6 mg/kg and above (i.e. total drug exposure regardless of starting dose and intermediary doses as long as the patient reached doses > 6 mg/kg)] (N=13) n (%) | Total (N=79) n (%) | STRENSIQ (N=20) n (%)
Injection site reactions | 38 (58) | 6 (46) | 44 (56) | 18 (90)
Erythema | 29 (44) | 3 (23) | 32 (41) | 15 (75)
Discoloration/ Hypopigmentation | 11 (17) | 1 (8) | 12 (15) | 8 (40)
Pain/ Tenderness | 10 (15) | 1 (8) | 11 (14) | 8 (40)
Pruritus/ Itching | 10 (15) | 0 (0) | 10 (13) | 7 (35)
Swelling | 8 (12) | 0 (0) | 8 (10) | 6 (30)
Induration | 9 (14) | 1 (8) | 10 (13) | 3 (15)
Macule | 4 (6) | 0 (0) | 4 (5) | 7 (35)
Reaction, not otherwise specified | 6 (9) | 1 (8) | 7 (9) | 4 (20)
Bruising | 6 (9) | 0 (0) | 6 (8) | 4 (20)
Nodule | 2 (3) | 0 (0) | 2 (3) | 2 (10)
Other injection site reactions [Other injection site reactions include injection site rash, inflammation, papule, hemorrhage, hematoma, urticaria, warmth, calcification, mass, scar and cellulitis.] | 10 (15) | 3 (23) | 13 (17) | 4 (20)
Ectopic calcifications | 3 (5) | 0 (0) | 3 (4) | 11 (55)
Lipodystrophy | 12 (18) | 2 (15) | 14 (18) | 14 (70)
Injection site atrophy | 4 (6) | 2 (15) | 6 (8) | 8 (40)
Injection site hypertrophy | 5 (8) | 0 (0) | 5 (6) | 6 (30)
Other lipodystrophy [Other lipodystrophy includes lipohypertrophy.] | 4 (6) | 0 (0) | 4 (5) | 1 (5)
Hypersensitivity reactions | 7 (11) | 3 (23) | 10 (13) | 2 (10)
Vomiting/emesis | 2 (3) | 2 (15) | 4 (5) | 2 (10)
Other hypersensitivity reactions [Other hypersensitivity reactions include erythema/redness, pyrexia/fever, irritability, nausea, pain, rigor/chills, hypoesthesia oral, headache, flushing, and anaphylaxis.] | 6 (9) | 2 (15) | 8 (10) | 2 (10)

Less Common Adverse Reactions

Adverse reactions that occurred at rates less than 1% included:

- Hypocalcemia
- Renal Stones
- Chronic hepatitis
- Decreased vitamin B6

Long-Term Safety

In long-term extension trials reflecting a median exposure to STRENSIQ of 142 weeks (range 0.1 weeks to 392 weeks) in 112 patients with perinatal/infantile- (n = 89), juvenile- (n = 22), and adult-onset (n = 1) HPP (age at enrollment = 1 day to 66.5 years), the most common adverse reactions were similar to those reported in Table 4.

6.2 Immunogenicity

As with all therapeutic proteins, there is potential for immunogenicity. The detection of antibody formation is highly dependent on the sensitivity and specificity of the assay. Additionally, the observed incidence of antibody (including neutralizing antibody) positivity in an assay may be influenced by several factors including assay methodology, sample handling, timing of sample collection, concomitant medications, and underlying disease. For these reasons, comparison of the incidence of the antibodies in the studies described below with the incidence of antibodies in other studies or to other asfotase alfa products may be misleading.

During clinical trials, anti-asfotase alfa antibodies have been detected in patients receiving treatment with STRENSIQ using an electrochemiluminescent (ECL) immunoassay. Antibody positive samples were tested to determine the presence of neutralizing antibodies based on in vitro inhibition of the catalytic activity of STRENSIQ.

Among STRENSIQ-treated patients with hypophosphatasia (HPP) in clinical studies who had post-baseline antibody data available, 97/109 (89%) tested positive for anti-asfotase alfa antibodies at some time point during STRENSIQ treatment. Among those 97 patients, 55 (57%) also tested positive for neutralizing antibodies at some time point during STRENSIQ treatment. No correlation was observed between the anti-asfotase alfa antibody titers and the neutralizing antibody (% inhibition) values. Formation of anti-asfotase alfa antibody resulted in a reduced systemic exposure of asfotase alfa [see Clinical Pharmacology (12.3)].

6.3 Postmarketing Experience

The following adverse reactions have been identified during post-approval use of STRENSIQ. Because these reactions are reported voluntarily from a population of uncertain size, it is not always possible to reliably estimate their frequency or establish a causal relationship to drug exposure.

Some STRENSIQ-treated patients with initial therapeutic response to STRENSIQ subsequently developed worsening in disease-associated laboratory and radiographic biomarkers (some in association with neutralizing antibodies) suggesting possible immune-mediated effects on STRENSIQ's pharmacologic action resulting in disease progression [see Warnings and Precautions (5.4)].

7 DRUG INTERACTIONS

7.1 Drug Interference with Laboratory Tests

Laboratory Tests Utilizing Alkaline Phosphatase as a Detection Reagent

Studies have shown that there is analytical interference between asfotase alfa and laboratory tests that utilize an alkaline phosphatase (ALP)-conjugated test system, rendering erroneous test results in patients treated with STRENSIQ. ALP-conjugated test systems are utilized to measure substances such as hormones, bacterial antigens and antibodies. Therefore, it is recommended that laboratory assays which do not have ALP-conjugate technology be used when testing samples from patients who are receiving STRENSIQ.

To avoid erroneous test results for patients treated with STRENSIQ, inform laboratory personnel that the patient is being treated with STRENSIQ and discuss the use of a testing platform which does not utilize an ALP-conjugated test system.

Serum Alkaline Phosphatase

High serum ALP measurements detected through clinical laboratory testing are expected in patients receiving STRENSIQ and reflect circulating concentrations of asfotase alfa.

Do not rely on serum ALP measurements for clinical decision making in patients treated with STRENSIQ.

8 USE IN SPECIFIC POPULATIONS

8.1 Pregnancy

Risk Summary

There are no available data on STRENSIQ use in pregnant women to inform a drug associated risk. In animal reproduction studies, asfotase alfa administered intravenously to pregnant rats and rabbits during the period of organogenesis showed no evidence of fetotoxicity, embryolethality or teratogenicity at doses causing plasma exposures up to 21 and 24 times, respectively, the exposure at the recommended human dose (see Data).

In the U.S. general population, the estimated background risk of major birth defects and miscarriage in clinically recognized pregnancies is 2 to 4% and 15 to 20%, respectively.

Data

Animal Data

Asfotase alfa administered during the period of organogenesis to rats (from gestation Day 6 to Day 19 post-partum) and rabbits (on gestation days 7 to 19) at intravenous doses up to 50 mg/kg/day, approximately 21 and 24 times the human AUC of 65486 ng.h/mL at 2 mg/kg dose administered three times weekly for a 50 kg individual, respectively did not cause any adverse effects on embryofetal development. A pre- and post-natal development study in pregnant rats showed no evidence of adverse effects on pre- and post-natal development at intravenous doses (from Day 6 of gestation to Day 19 postpartum) of asfotase alfa up to 50 mg/kg/day approximately 21 times the human AUC of 65486 ng.h/mL at 2 mg/kg dose administered three times weekly for a 50 kg individual.

8.2 Lactation

Risk Summary

There are no data on the presence of asfotase alfa in human milk, the effects on the breastfed infant, or the effects on milk production. The developmental and health benefits of breastfeeding should be considered along with the mother's clinical need for STRENSIQ and any potential adverse effects on the breastfed infant from asfotase alfa or from the underlying maternal condition.

8.4 Pediatric Use

The safety and effectiveness of STRENSIQ for the treatment of perinatal/infantile- and juvenile-onset HPP have been established in pediatric patients. Use of STRENSIQ for this indication is based on 4 prospective, open-label clinical trials conducted in 89 pediatric patients with perinatal/infantile-onset or juvenile-onset HPP [see Clinical Studies (14)].

8.5 Geriatric Use

No patients with perinatal/infantile- or juvenile-onset HPP aged 65 years were enrolled in clinical trials of STRENSIQ. Therefore, there is no information available to determine whether patients aged 65 years and over respond differently from younger patients.

11 DESCRIPTION

Asfotase alfa is a tissue nonspecific alkaline phosphatase (TNSALP) produced by recombinant DNA technology in a Chinese hamster ovary cell line. Asfotase alfa is a soluble glycoprotein composed of two identical polypeptide chains. Each chain contains 726 amino acids with a theoretical mass of 161 kDa. Each chain consists of the catalytic domain of human TNSALP, the human immunoglobulin G1 Fc domain and a deca-aspartate peptide used as a bone targeting domain. The two polypeptide chains are covalently linked by two disulfide bonds.

STRENSIQ (asfotase alfa) injection is a sterile, preservative-free, nonpyrogenic, clear, slightly opalescent or opalescent, colorless to slightly yellow, with few small translucent or white particles, aqueous solution for subcutaneous administration. STRENSIQ is supplied in glass single-dose vials containing asfotase alfa; dibasic sodium phosphate, heptahydrate; monobasic sodium phosphate, monohydrate; and sodium chloride at a pH between 7.2 and 7.6. Table 5 describes the content of STRENSIQ vial presentations.

Table 5: Content of STRENSIQ Vial Presentations
Ingredient | Quantity per Vial
Asfotase Alfa | 18 mg/0.45 mL | 28 mg/0.7 mL | 40 mg/mL | 80 mg/0.8 mL
Dibasic sodium phosphate, heptahydrate | 2.48 mg | 3.85 mg | 5.5 mg | 4.4 mg
Monobasic sodium phosphate, monohydrate | 0.28 mg | 0.43 mg | 0.62 mg | 0.5 mg
Sodium chloride | 3.94 mg | 6.13 mg | 8.76 mg | 7.01 mg

12 CLINICAL PHARMACOLOGY

12.1 Mechanism of Action

HPP is caused by a deficiency in TNSALP enzyme activity, which leads to elevations in several TNSALP substrates, including inorganic pyrophosphate (PPi). TNSALP is a metallo-enzyme that catalyzes the hydrolysis of phosphomonoesters with release of inorganic phosphate and alcohol. Elevated extracellular levels of PPi block hydroxyapatite crystal growth which inhibits bone mineralization and causes an accumulation of unmineralized bone matrix which manifests as rickets and bone deformation in infants and children and as osteomalacia (softening of bones) once growth plates close, along with muscle weakness. Replacement of the TNSALP enzyme upon STRENSIQ treatment reduces the enzyme substrate levels.

12.2 Pharmacodynamics

Perinatal/infantile- and juvenile-onset HPP patients treated with STRENSIQ had reductions in plasma TNSALP substrates, PPi and pyridoxal 5'-phosphate (PLP) within 6 to 12 weeks of treatment. Reductions in plasma PPi and PLP levels did not correlate with clinical outcomes.

Bone biopsy data from perinatal/infantile-onset and juvenile-onset HPP patients treated with STRENSIQ demonstrated decreases in osteoid volume and thickness indicating improved bone mineralization.

12.3 Pharmacokinetics

Based on data in 38 HPP patients, the pharmacokinetics of asfotase alfa exhibit dose proportionality across the dose range of 0.3 mg/kg to 3 mg/kg once every other day (three times a week) and appear to be time-independent. Steady state exposure was achieved as early as three weeks after the administration of the first dose. The elimination half-life following subcutaneous administration was approximately 5 days.

Table 6 summarizes the pharmacokinetic parameters following multiple doses in 20 HPP patients after subcutaneous administration of STRENSIQ at 2 mg/kg three times per week in Study 2 (age of less than or equal to 5 years) and Study 3 (age of greater than 5 to 12 years), indicating the pharmacokinetics were similar between patients in the two age groups.

Table 6: Summary of Pharmacokinetic Parameters Following Multiple Subcutaneous Administration of STRENSIQ 2 mg/kg Three Times per Week
 | Study 2 | Study 3
N | 14 | 6
Age (year) | 3.4 ± 2.1 (0.2, 6.2) | 8.6 ± 2.2 (6.1, 12.6)
Weight at baseline (kg) | 11.2 ± 5.0 (2.9, 17.1) | 21.2 ± 7.9 (11.4, 35.4)
tlast (h) | 48.1 ± 0.1 (47.9, 48.3) | 48.0 ± 0.1 (48.0, 48.1)
tmax (h) | 14.9 ± 10.4 (0, 32.2) | 20.8 ± 10.0 (11.9, 32.2)
Cmax (ng/mL) | 1794 ± 690 (856, 3510) | 2108 ± 788 (905, 3390)
AUCt (h*ng/mL) | 66042 ± 25758 (27770, 119122) | 89877 ± 33248 (37364, 142265)
Accumulation Ratio [Ratio values reflect the fold increase of AUCt from Week 1 based on mean AUCt, values.] | 1.5 | 3.9
Data are presented as mean ± standard deviation (range). Study 3 includes patients with perinatal/infantile- or juvenile-onset of disease. tlast, time of last concentration; tmax, time of maximal concentration; Cmax, maximal concentration; AUCt, area under the concentration-time curves over a dosing interval of 48 hours

Population PK analysis of asfotase alfa concentrations supports weight-based dosing because body weight is a major covariate of asfotase alfa clearance. The formulation concentration had an impact on the systemic exposure of asfotase alfa in HPP patients. The higher concentration formulation (80 mg/0.8 mL vial) achieved an approximately 25% lower systemic asfotase alfa exposure (i.e., concentrations and AUC) compared to the lower concentration formulations (18 mg/0.45 mL, 28 mg/0.7 mL or 40 mg/mL vials) at the same dose of STRENSIQ [see Dosage and Administration (2.2)].

Anti-Drug Antibody Effects on Pharmacokinetics

Formation of anti-drug antibodies resulted in reduced systemic exposure of asfotase alfa.

13 NONCLINICAL TOXICOLOGY

13.1 Carcinogenesis, Mutagenesis, Impairment of Fertility

Long-term studies in animals to evaluate carcinogenic potential or studies to evaluate mutagenic potential have not been performed with asfotase alfa. Asfotase alfa at intravenous doses up to 50 mg/kg/day administered daily in pregnant rats (approximately 21 times the human AUC of 65486 ng.h/mL at 2 mg/kg dose administered three times weekly for a 50 kg individual) was found to have no adverse effect on fertility and reproductive performance of male and female rats.

14 CLINICAL STUDIES

14.1 Perinatal/Infantile-Onset HPP

Study 1 was a 24-week prospective single-arm trial in 11 patients with severe perinatal/infantile-onset HPP. In this study, 7/11 (64%) were female and 10/11 (91%) patients were white, and age ranged from 3 weeks to 39.5 months. Severe perinatal/infantile-onset HPP was defined as biochemical, medical history and radiographic evidence of HPP as well as the presence of any of the following: rachitic chest deformity, vitamin B6-dependent seizures, or failure to thrive. Ten of 11 patients completed the 24-week trial and continued treatment in the extension phase. Nine patients have been treated for at least 216 weeks (54 months) and 4 patients have been treated for over 240 weeks (60 months). Patients received subcutaneous STRENSIQ 3 mg/kg per week for the first month; subsequently, dose increases up to 9 mg/kg per week were allowed for changes in weight and/or for lack of efficacy. All 10 patients required dose increases up to 6 mg/kg per week or higher; 9 patients increased between 4 and 24 weeks after starting treatment and 1 patient increased after 70 weeks due to suboptimal clinical response. One patient's dose was decreased from 9 mg/kg per week to 6 mg/kg per week based on PK data.

Study 2 was a prospective open-label study in 59 patients with perinatal/infantile-onset HPP. In this study, 32/59 (54%) were female, 46/59 (78%) were white, and age ranged from 1 day to 78 months. Patients received subcutaneous STRENSIQ at 6 mg/kg per week for the first 4 weeks. Ten patients received dose increases higher than 6 mg/kg per week due to suboptimal clinical response, with dose increases occurring between 8 and 24 weeks after starting treatment. The recommended dosage regimen of STRENSIQ for the treatment of perinatal/infantile-onset HPP is up to 9 mg/kg per week administered subcutaneously as 3 mg/kg three times per week [see Dosage and Administration (2.2)].

Forty-one patients were treated for at least 24 weeks (6 months) and 15 patients were treated for at least 96 weeks (24 months).

Survival and Ventilation-Free Survival in Perinatal/Infantile-Onset HPP

Survival and invasive ventilation-free survival were compared in STRENSIQ-treated patients (Studies 1 and 2) with a historical cohort of untreated patients with similar clinical characteristics (Table 7 and Figure 1).

Table 7: Survival and Invasive Ventilation-Free Survival in STRENSIQ-Treated versus Historical Control Patients with Perinatal/ Infantile-Onset HPP (Pooled Studies 1 and 2)
 | STRENSIQ-Treated | Historical Controls
Survival | n = 68 | n = 48
Alive at Point of Last Contact (%) | 91 | 27
Hazard Ratio (STRENSIQ/Historical Control), 95% Confidence Interval [Adjusted for year of diagnosis.] | 0.14 (0.05, 0.39)
Kaplan-Meier Estimate and Alive at Age 1 Year (Week 48) (%) | 97 | 42
Invasive Ventilation-Free Survival [Alive and not initiating invasive ventilation after start of STRENSIQ treatment. STRENSIQ-treated patients on invasive ventilation at baseline were excluded from this analysis.] | n = 54 | n = 48
Alive and Not on Ventilation at Point of Last Contact (%) | 85 | 25
Hazard Ratio (STRENSIQ/Historical Control), 95% Confidence Interval | 0.21 (0.09, 0.51)
Kaplan-Meier Estimate of Alive and Not on Ventilation at Age 1 Year (Week 48) (%) | 96 | 31

In patients who required any form of respiratory support, 21 of 26 (81%) of the treated patients survived through their last assessment (median age at last assessment was 3.2 years of age), versus 1 of 20 (5%) of historical controls.

Figure 1: Overall Survival in STRENSIQ-Treated versus Historical Control Patients with Perinatal/ Infantile-Onset HPP (Pooled Studies 1 and 2)

Skeletal Manifestations in Perinatal/Infantile-Onset HPP

Radiographs from 68 STRENSIQ-treated perinatal/infantile-onset HPP patients, including 64 patients in Studies 1 and 2, and 4 patients in Study 3 [see Clinical Studies (14.2)], were examined to assess HPP-related rickets using the 7-point Radiographic Global Impression of Change (RGI-C) scale. Patients with a minimum RGI-C score of +2 were defined as "responders". Radiologic improvements could be seen by Month 24; at last assessment, 50/68 [74%] treated patients were rated as RGI-C responders. No comparative data were available from historical controls. The mean time interval between the baseline and last RGI-C assessment was 24 months (range was 1 month to 67 months).

Eighteen perinatal/infantile-onset HPP patients experienced fractures during the course of treatment. There were insufficient data to determine the effect of STRENSIQ on fractures.

Growth in Perinatal/Infantile-Onset HPP

Height and weight measurements (as measured by Z-scores) were available post-treatment for 72 perinatal/infantile-onset HPP patients, including 68 patients enrolled in Studies 1 and 2, and 4 patients enrolled in Study 3 (Table 8).

Table 8: Perinatal/Infantile-Onset Height and Weight Measurements as Measured by Z-Score (Studies 1 and 2)
 | Height Z-score |  |  |  | Weight Z-score
 | Baseline |  | Last Assessment |  | Baseline |  | Last Assessment
 | Mean | Min, Max | Mean | Min, Max | Mean | Min, Max | Mean | Min, Max
Studies 1 and 2 [The mean time interval between baseline and last assessment was 21 months (range was 1 month to 72 months).] (N=68) | -3.3 | -10.1, 0.9 | -2.9 | -10.6, 0.4 | -3.2 | -23.8, 0 | -2.4 | -20.9. 1.1
Study 3 (N=4) [The mean time between baseline and last assessment was 56 months (range was 53 months to 60 months).] | -2.6 | -6.6, -0.7 | -1.5 | -5.8, 0.4 | -2.5 | -8.2, -1.0 | -1.5 | -5.4, 0.5

Long-Term Extension Trials in Perinatal/Infantile-Onset HPP

Long-term data were collected in 68 STRENSIQ-treated patients with perinatal/infantile onset HPP in Studies 1 and 2 and an additional 10 patients enrolled in Study 2. The longest duration of follow-up in the 78 patients was 7 years (84 months). At point of last contact, 69/78 (88%) STRENSIQ-treated patients had survived.

14.2 Juvenile-Onset HPP

Study 3 was a prospective open-label 24-week trial that included 8 juvenile-onset HPP patients and 5 perinatal/ infantile-onset HPP patients; 11/13 (85%) were male and 12/13 (92%) were white [see Clinical Studies (14.1)]. On study entry, patients were 6 to 12 years of age. All 8 juvenile-onset patients entered the extension study and were treated for at least 48 months. At trial entry, patients were randomized to receive subcutaneous STRENSIQ 6 mg/kg per week or 9 mg/kg per week. Two patients received dose reductions during the primary treatment period, including one patient who experienced a decrease in vitamin B6 levels and one patient who experienced recurrent injection site reactions. During the extension phase, the dosing regimen for all patients was initially changed to 3 mg/kg per week. Dosing was subsequently increased to 6 mg/kg per week, with no patients requiring doses higher than 6 mg/kg per week. The recommended dosage regimen of STRENSIQ for the treatment of juvenile-onset HPP is 6 mg/kg per week [see Dosage and Administration (2.2)].

Growth in Juvenile-Onset HPP

Height and weight measurements (as measured by Z-scores) in 8 STRENSIQ-treated juvenile-onset HPP patients were compared with a historical cohort of 32 untreated patients with similar clinical characteristics (Table 9). Height and weight data for historical patients were collected from medical records.

Table 9: Juvenile-Onset Height and Weight Measurements as Measured by Z-Score (Study 3)
 | Height Z-score |  |  |  | Weight Z-score
 | Baseline |  | Last Assessment |  | Baseline |  | Last Assessment
 | Mean | Min, Max | Mean | Min, Max | Mean | Min, Max | Mean | Min, Max
STRENSIQ (N=8) [The mean time interval between baseline and last assessment was 55 months (range was 53 months to 60 months).] | -1.5 | -3.8, 0 | -0.9 | -2, 0 | -1.1 | -3.5, 2.3 | 0 | -1.3, 2.2
Control (N=32) [The mean time interval between baseline and last assessment was 61 months (range was 19 months to 109 months).] | -1.1 | -4.9, 2.6 | -1.1 | -4.9, 1.8 | -1.2 | -5, 2.1 | -1 | -5.7, 2.1

Skeletal Manifestations in Juvenile-Onset HPP

Radiographs from 8 STRENSIQ-treated juvenile-onset HPP patients and 32 historical controls were compared to assess HPP-related rickets using the 7-point RGI-C (Radiographic Global Impression of Change) scale. Patients who achieved a RGI-C score of 2 or higher (corresponding to substantial healing of rickets) were classified as being responders to treatment. All 8 treated patients were rated as responders by Month 54 of treatment. The mean duration between the baseline and last RGI-C assessments for control patients was 56 months (range was 8 to 95 months). At last assessment, 2/32 (6%) of control patients were rated as responders.

Eight of 20 (40%) patients with juvenile-onset HPP experienced new fractures during the course of treatment. There were insufficient data to assess the effect of STRENSIQ on fractures.

Gait/Mobility in Juvenile-Onset HPP

Gait was assessed using a modified Performance Oriented Mobility Assessment-Gait (MPOMA-G) scale in 8 STRENSIQ-treated juvenile-onset HPP patients at 6-month intervals out to 36 months. Mobility was also assessed using the 6 Minute Walk Test (6MWT) in 7 of the 8 patients. Step length improved by at least 1 point in either foot in 6/8 patients compared to 1/6 (17%) control patients. The proportion of patients who had 6MWT percent predicted values within the normal range for age, sex, and height-matched peers increased from 0/8 patients at baseline to 6/6 patients (100%) by Month 48 and all 6 were also able to walk longer distances at this time point compared to baseline.

Long-Term Extension Trials in Juvenile-Onset HPP

Long-term data were collected in 8 patients with juvenile-onset HPP treated with STRENSIQ for at least 6 years (72 months). At last assessment, 7 patients with available 6MWT results had maintained improvements in gait/mobility.

16 HOW SUPPLIED/STORAGE AND HANDLING

STRENSIQ is supplied as a sterile, nonpyrogenic, preservative-free, clear, slightly opalescent or opalescent, colorless to slightly yellow aqueous solution; a few small translucent or white particles may be present. The product is available as single-dose vials in a carton of one (1) or twelve (12) vials at the following strengths:

Table 10: STRENSIQ Vial Presentations
Strength | National Drug Code (NDC) | Quantity of Vials in Carton
18 mg/0.45 mL | NDC 25682-010-01 | 1
18 mg/0.45 mL | NDC 25682-010-12 | 12
28 mg/0.7 mL | NDC 25682-013-01 | 1
28 mg/0.7 mL | NDC 25682-013-12 | 12
40 mg/mL | NDC-25682-016-01 | 1
40 mg/mL | NDC-25682-016-12 | 12
For pediatric patients 40 kg and greater
80 mg/0.8 mL | NDC 25682-019-01 | 1
80 mg/0.8 mL | NDC 25682-019-12 | 12

STORAGE AND HANDLING

STRENSIQ vials must be stored in the original carton until the time of use under refrigerated conditions at 2°C to 8°C (36°F to 46°F) and protected from light.

Once removed from refrigeration, STRENSIQ should be administered within 3 hours.

Do not use beyond the expiration date stamped on the carton.

DO NOT FREEZE OR SHAKE.

Vials are for one time use only. Discard any unused product.

17 PATIENT COUNSELING INFORMATION

Advise the patient or caregiver to read the FDA-approved patient labeling (Patient Information and Instructions for Use).

Advise patients or caregivers of the following:

Preparation

- When preparing a volume for injection greater than 1 mL, split the volume equally between two syringes, and administer two injections. When administering the two injections, use two separate injection sites.
- Take the unopened STRENSIQ vial(s) out of the refrigerator 15 to 30 minutes before injecting to allow the liquid to reach room temperature.
- Inspect the solution in the vial(s) for particulate matter and discoloration.
- Assemble injection supplies. Administer STRENSIQ using sterile disposable syringes and injection needles. The syringes should be of small enough volume that the prescribed dose can be withdrawn from the vial with reasonable accuracy. Always use a new syringe and needle.
- Remove vial cap, aseptically prepare the vial and insert the syringe into the vial to withdraw the prescribed dose for administration.
- Remove any air bubbles in the syringe and verify the correct dose.
- STRENSIQ vials are for one time use only. Discard any unused product [see Dosage and Administration (2.4)].

Administration

- Administer STRENSIQ within 3 hours upon removal of the vial(s) from refrigeration.
- Rotate the injection site to reduce the risk of lipohypertrophy and injection site atrophy.
- Do NOT administer injections in areas that are reddened, inflamed, or swollen.
- Inject STRENSIQ subcutaneously into the determined site and properly dispose of the syringe and needle [see Dosage and Administration (2.5)].

Hypersensitivity Reactions Including Anaphylaxis

- Life-threatening hypersensitivity reactions, including anaphylaxis may occur with STRENSIQ treatment.
- Anaphylaxis has occurred during the early course of enzyme replacement therapy and after extended duration of therapy.
- Symptoms of life-threatening hypersensitivity reactions, including anaphylaxis and to seek immediate medical care should symptoms occur [see Warnings and Precautions (5.1)].

Lipodystrophy

- Lipohypertrophy (enlargement or thickening of tissue) and localized atrophy (depression in the skin) have been reported at injection sites after several months. Follow proper injection technique and rotate injection sites [see Warnings and Precautions (5.2)].

Possible Immune-Mediated Clinical Effects

- Anti-drug antibodies may develop during treatment which may interfere with STRENSIQ's pharmacologic action. Inform patients or their caregivers to contact their healthcare provider if they experience worsening symptoms of HPP (e.g., increased respiratory support, increased difficulty walking, new fractures) [see Warnings and Precautions (5.4)].

Hypophosphatasia (HPP) Registry

- A registry has been established in order to better understand HPP in the population, and to monitor and evaluate long-term treatment effects of STRENSIQ. Patients and their caregivers should be encouraged to participate and advised that their participation is voluntary and may involve long-term follow-up. For more information, visit www.hppregistry.com

Manufactured by:
Alexion Pharmaceuticals, Inc.
121 Seaport Boulevard
Boston, MA 02210 USA

U.S. License Number: 1743

STRENSIQ is a trademark of Alexion Pharmaceuticals, Inc.
© 2024 Alexion Pharmaceuticals, Inc.

PATIENT INFORMATION
STRENSIQ® [stren sik]
(asfotase alfa)
injection, for subcutaneous use

What is the most important information I should know about STRENSIQ?
STRENSIQ may cause serious side effects, including:

- severe allergic (hypersensitivity) reactions. Allergic reactions are common with STRENSIQ treatment and can be severe and life-threatening. Severe allergic reactions have happened in some people within minutes after receiving STRENSIQ and more than 1 year after starting treatment with STRENSIQ. Stop using STRENSIQ and go to the nearest hospital emergency room right away if you get any of the following signs and symptoms of a serious allergic reaction:

- difficulty breathing
- choking sensation
- swelling of your eyes, lips, or tongue
- dizziness
- nausea or vomiting
- fever
- headache

- sweating
- feeling irritable
- chills
- skin redness
- skin rash or hives
- itching or numbness of the tongue, lips, cheeks, or gums

What is STRENSIQ?
STRENSIQ is a prescription medicine used to treat people with perinatal, infantile, and juvenile onset hypophosphatasia (HPP).

Before using STRENSIQ, tell your healthcare provider about all of your medical conditions, including if you:

- have had an allergic reaction to STRENSIQ.
- are pregnant or plan to become pregnant. It is not known if STRENSIQ will harm your unborn baby.
- are breastfeeding or plan to breastfeed. It is not known if STRENSIQ passes into your breast milk. Talk to your healthcare provider about the best way to feed your baby if you use STRENSIQ.

Tell your healthcare provider about all the medicines you take, including prescription and over-the-counter medicines, vitamins, and herbal supplements.

There is a registry for people who use STRENSIQ. The purpose of this registry is to collect information about HPP and about what happens when you use STRENSIQ for a long time. For more information about this registry, talk with your healthcare provider or go to www.hppregistry.com.

How should I use STRENSIQ?

- Use STRENSIQ exactly as your healthcare provider tells you to.
- You will begin receiving STRENSIQ under the supervision of a healthcare provider.
- See the "Instructions for Use" at the end of the Patient Information for instructions about:
  - How to prepare and inject STRENSIQ
  - How to properly throw away (dispose of) any unused STRENSIQ
  - How to dispose of used syringes and needles.
- Your healthcare provider will tell you how much STRENSIQ to use and when to use it.
- Your healthcare provider may change your dose, if needed.

What are the possible side effects of STRENSIQ?

STRENSIQ may cause serious side effects, including:

- severe allergic (hypersensitivity) reactions. See "What is the most important information I should know about STRENSIQ?"
- skin thickening or pits at the injection site (lipodystrophy). Lipodystrophy is common and has happened after several months in people treated with STRENSIQ.
- calcium build-up in your eyes and kidneys. People with HPP are at increased risk for developing calcium build-up in the body. Calcium build-up in the eyes and kidneys has happened and is a common side effect of STRENSIQ. Calcium build-up in the eyes and kidneys may also happen in people with HPP who are not treated with STRENSIQ. Your healthcare provider should check your eyes and kidneys before and during treatment with STRENSIQ.
- immune-related effects. You may develop antibodies during treatment that may decrease how well STRENSIQ works. Tell your healthcare provider right away if you get worsening symptoms of HPP including:

- difficulty breathing
- difficulty walking
- feeling tired

- bone pain
- stiff joints
- loss of appetite

The most common side effects of STRENSIQ include local skin injection site reactions such as skin redness, bruising, color change, pain, itching, hardening of the skin (induration), swelling, and bumps.

These are not all of the possible side effects of STRENSIQ. For more information, ask your healthcare provider or pharmacist.
Call your doctor for medical advice about side effects. You may report side effects to FDA at 1-800-FDA-1088.

General information about the safe and effective use of STRENSIQ.

Medicines are sometimes prescribed for purposes other than those listed in a Patient Information leaflet. Do not use STRENSIQ for a condition for which it was not prescribed. Do not give STRENSIQ to other people, even if they have the same symptoms that you have. It may harm them. You can ask your pharmacist or healthcare provider for information about STRENSIQ that is written for health professionals.

What are the ingredients in STRENSIQ?

Active ingredient: asfotase alfa.
Inactive ingredients: dibasic sodium phosphate, heptahydrate; monobasic sodium phosphate, monohydrate and sodium chloride.

Manufactured by: Alexion Pharmaceuticals, Inc., Boston, MA 02210 USA
U.S. License Number: 1743
For more information, go to www.strensiq.com or call 888-765-4747.

This Patient Information has been approved by the U.S. Food and Drug Administration.

Revised: 7/2024

INSTRUCTIONS FOR USE STRENSIQ® [stren' sik] (asfotase alfa) injection, for subcutaneous use vial

Read this "Instructions for Use" before you start using STRENSIQ and each time you get a refill. There may be new information. This information does not take the place of talking to your healthcare provider about your medical condition or your treatment.

Do not share your syringes or needles with anyone else. You may give an infection to them or get an infection from them.

Supplies needed to give your STRENSIQ injection (See Figure A):

- 1 or 2 STRENSIQ vial(s).
- 1 or 2 sterile disposable 1 mL syringes for injection with 25 to 29 gauge (G), ½ inch needles.
  - The use of two different gauge needles is recommended, a larger bore needle (e.g. 25 gauge) for withdrawal of the medication, and a smaller bore needle (e.g. 29 gauge) for the injection.
  - Always use a new syringe and needle for each injection.
- 2 alcohol wipes
- 1 gauze or cotton ball
- a clean flat surface, like a table
- 1 sharps container for throwing away used needles and syringes. See "Disposing of used needles and syringes" at the end of these instructions.

Figure A

Storing your STRENSIQ dose:

- Store STRENSIQ in the original carton in the refrigerator between 36°F to 46°F (2°C to 8°C) until you are ready to use it.
- Do not freeze your STRENSIQ vials. Do not use STRENSIQ if it has been frozen.
- Do not shake your STRENSIQ vials.
- Protect STRENSIQ from light until you are ready to use it.
- Do not use STRENSIQ after the expiration date printed on the carton.
- STRENSIQ vials are for 1 time use only. Throw away any unused STRENSIQ left in the vial.

Preparing your STRENSIQ dose and giving your STRENSIQ injection:

- Prepare a clean flat surface, like a table or counter top.
- Remove the unopened STRENSIQ vial(s) out of the refrigerator and allow it to sit at room temperature for at least 15 to 30 minutes. Injecting STRENSIQ when cold can make the injection feel uncomfortable.
  - Do not warm STRENSIQ in any way other than letting it sit at room temperature (for example, do not warm it in a microwave or in hot water).
- Gather all the supplies you will need to give your STRENSIQ injection.
- Wash your hands with soap and water.
- Utilize STRENSIQ within 3 hours after removing it from the refrigerator.
- Inject STRENSIQ exactly as your healthcare provider has shown you.

Step 1: | Check the liquid in the STRENSIQ vial. STRENSIQ liquid should look clear or slightly yellow and may have a few small white particles in it. Do not use it if the liquid is discolored or contains any lumps or large particles in it. Throw it away and get a new vial.
Step 2: | Using your thumb, flip the plastic cap off the STRENSIQ vial.
Step 3: | Remove the larger bore needle (e.g., 25 G) from the package. Pick up the syringe and place the needle on the tip of the syringe. Push down and twist the needle onto the syringe until it is tight.
Step 4: | Hold the syringe with the needle pointing up and pull back the plunger until the top of the plunger reaches the line for your prescribed dose.
Step 5: | Pull the cap straight off of the needle.; - Do not touch the needle or let the needle touch any surface.
Step 6: | Hold the STRENSIQ vial firmly on a flat surface, then push the needle through the rubber stopper of the STRENSIQ vial.
Step 7: | Keeping the needle in the STRENSIQ vial, lift the vial and turn it upside down with the needle pointing toward the ceiling. Slowly push the plunger all the way in.
Step 8: | With the needle tip still in the liquid, slowly pull back the plunger until the top of the plunger reaches the line slightly past the line for your prescribed dose. Do not pull the needle out of the STRENSIQ vial. Slowly push the plunger up until the top of the plunger reaches the line for your prescribed dose.; - Check the syringe to make sure that you have the right dose.
Step 9: | Turn the STRENSIQ vial upright and pull the syringe straight out of the vial's rubber stopper.; - Do not touch the needle or allow the needle to touch any surface.; Carefully remove the larger bore needle (e.g., 25 G) you withdrew the STRENSIQ dose with and dispose of properly (as noted at the end of these instructions). Replace with a new, smaller bore needle (e.g., 29 G) prior to injection.
Step 10: | Hold the syringe with the needle pointing up and tap the barrel of the syringe with your finger to remove any air bubbles.
Step 11: | Choose your injection site. STRENSIQ is injected under the skin (subcutaneously) of your stomach-area (abdomen), upper arms, upper legs, or buttocks.; - Do not inject STRENSIQ into the buttocks for infants. - Change (rotate) your injection site with each injection. Do not use the same injection site for each injection. - Do not inject STRENSIQ into skin that is red, hot, or swollen. - Wipe your skin with an alcohol wipe. Let the site dry before you inject your dose.
Step 12: | Pinch the skin. Hold the syringe at a 90° angle (straight up and down) and insert the needle into your skin. For patients with little fat, hold the syringe at a 45° angle and insert the needle into your skin.
Step 13: | Push the plunger slowly and steadily all the way in to give your dose.
Step 14: | Pull the needle out of your skin.; - If you see blood after you take the needle out of your skin, press your injection site with a piece of gauze or alcohol wipe. - Do not recap the needle. Recapping the needle can lead to a needle stick injury.; If you need a second injection for your prescribed dose, get another STRENSIQ vial and repeat steps 1 through 14.

Disposing of used needles and syringes:

- Put your used needles in a FDA-cleared sharps disposal container right away after use. Do not throw away (dispose of) loose needles and syringes in your household trash.
- If you do not have a FDA-cleared sharps disposal container, you may use a household container that is:
  - made of a heavy-duty plastic,
  - can be closed with a tight-fitting, puncture-resistant lid,
  - without sharps being able to come out,
  - upright and stable during use,
  - leak-resistant, and
  - properly labeled to warn of hazardous waste inside the container.
- When your sharps disposal container is almost full, you will need to follow your community guidelines for the right way to dispose of your sharps disposal container. There may be state or local laws about how you should throw away used needles and syringes. For more information about safe sharps disposal, and for specific information about sharps disposal in the state that you live in, go to the FDA's website at: http://www.fda.gov/safesharpsdisposal.
- Do not dispose of your used sharps disposal container in your household trash unless your community guidelines permit this. Do not recycle your used sharps disposal container.

Keep STRENSIQ and all medicines, needles and syringes out of the reach of children.

This "Instructions for Use" has been approved by the U.S. Food and Drug Administration.

Manufactured by:

Alexion Pharmaceuticals, Inc.
Boston, MA 02210 USA
U.S. License Number: 1743

Approved: 6/2020

© 2020 Alexion Pharmaceuticals, Inc.

Printed in USA

PRINCIPAL DISPLAY PANEL - 18 mg/0.45 mL Vial Carton

NDC 25682-010-12
Rx only

STRENSIQ®
(asfotase alfa)
Injection

18 mg/0.45 mL

For Subcutaneous Use Only.

Single Use Only. Discard Unused Portion.
Do not mix or dilute with any solutions.
Must be Refrigerated.
Carton contains twelve (12) single-use
vials of 18 mg/0.45 mL.

PRINCIPAL DISPLAY PANEL - 28 mg/0.7 mL Vial Carton

NDC 25682-013-12
Rx only

STRENSIQ®
(asfotase alfa)
Injection

28 mg/0.7 mL

For Subcutaneous Use Only.

Single Use Only. Discard Unused Portion.
Do not mix or dilute with any solutions.
Must be Refrigerated.
Carton contains twelve (12) single-use
vials of 28 mg/0.7 mL.

PRINCIPAL DISPLAY PANEL - 40 mg/mL Vial Carton

NDC 25682-016-12
Rx only

STRENSIQ®
(asfotase alfa)
Injection

40 mg/mL

For Subcutaneous Use Only.

Single Use Only. Discard Unused Portion.
Do not mix or dilute with any solutions.
Must be Refrigerated.
Carton contains twelve (12) single-use
vials of 40 mg/mL.

PRINCIPAL DISPLAY PANEL - 80 mg/0.8 mL Vial Carton

NDC 25682-019-12
Rx only

STRENSIQ®
(asfotase alfa)
Injection

80 mg/0.8 mL

For Subcutaneous Use Only.

For patients 40 kg and greater.

Single Use Only. Discard Unused Portion.
Do not mix or dilute with any solutions.
Must be Refrigerated.
Carton contains twelve (12) single-use
vials of 80 mg/0.8 mL.